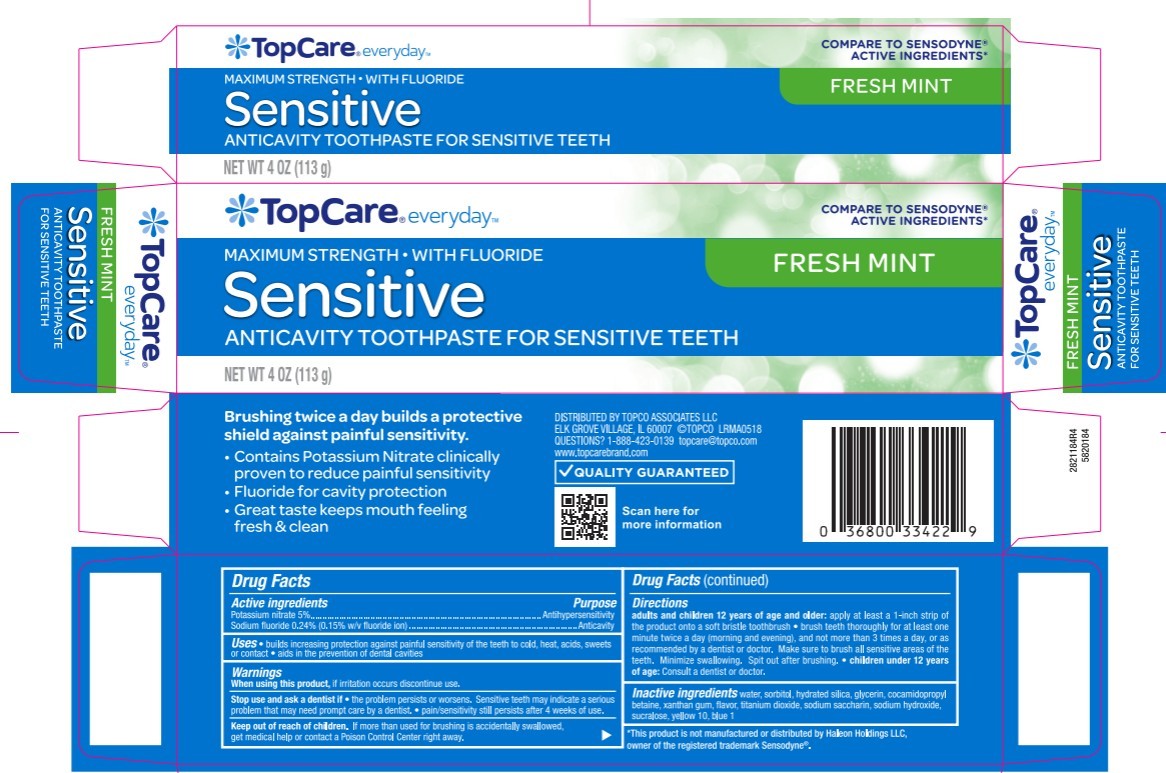 DRUG LABEL: Topco Associates LLC
NDC: 36800-364 | Form: PASTE, DENTIFRICE
Manufacturer: Topco Associates LLC
Category: otc | Type: HUMAN OTC DRUG LABEL
Date: 20250808

ACTIVE INGREDIENTS: SODIUM FLUORIDE 0.15 g/100 g; POTASSIUM NITRATE 5 g/100 g
INACTIVE INGREDIENTS: FD&C BLUE NO. 1; WATER; SACCHARIN SODIUM; SORBITOL; TITANIUM DIOXIDE; GLYCERIN; XANTHAN GUM; HYDRATED SILICA; SODIUM HYDROXIDE; COCAMIDOPROPYL BETAINE; SUCRALOSE; D&C YELLOW NO. 10

5820184 Topco Max Str Sens Mint (80-15206 upd)

Inactive ingredients

water, sorbitol, hydrated silica, glycerin, cocamidopropyl betaine, xanthan gum, flavor, titanium dioxide, sodium saccharin, sodium hydroxide, sucralose, yellow 10, blue 1

Directions

Adults and children 12 years of age and older: apply at least a 1-inch strip of product onto a soft bristle toothbrush

- brush teeth thoroughly for at least one minute twice a day (morning and evening), and not more than 3 tims a day, or as recommended by a dentist or doctor. Make sure to brush all sensitive areas of the teeth. Minimiza swallowing. Spit out after brushing.
- children under 12 years of age: Consult a dentist or doctor.

Uses

- builds increasing protection against painful sensitivity of the teeth to cold, heat, acids, sweets or contact
- aids in the prevention of dental cavities

When using this product, if irritation occurs discontinue use.

Stop use and ask a dentist if

- the problem persists or worsen
- Sensitive teeth may indicate a resious problem that may need prompt care by a dentist.
- pain/sensitivity still persists after 4 weeks of use

Keep out of reach of children. If more than used for burshing is accidentally swallowed, get medical help or contact a Poison Center right away.

Active ingredients / Purpose

Potassium nitrate 5%....................................................Antihypersensitivity

Sodium fluoride 0.24% (0.15% w/v fluoride ion)............Anticavity

DOSAGE AND ADMINISTRATION

adults and children 12 years of age and older: apply at least a 1-inch strip of the product onto a soft bristle toothbrush. Children under 12 years of age:consult a dentist or a doctor.